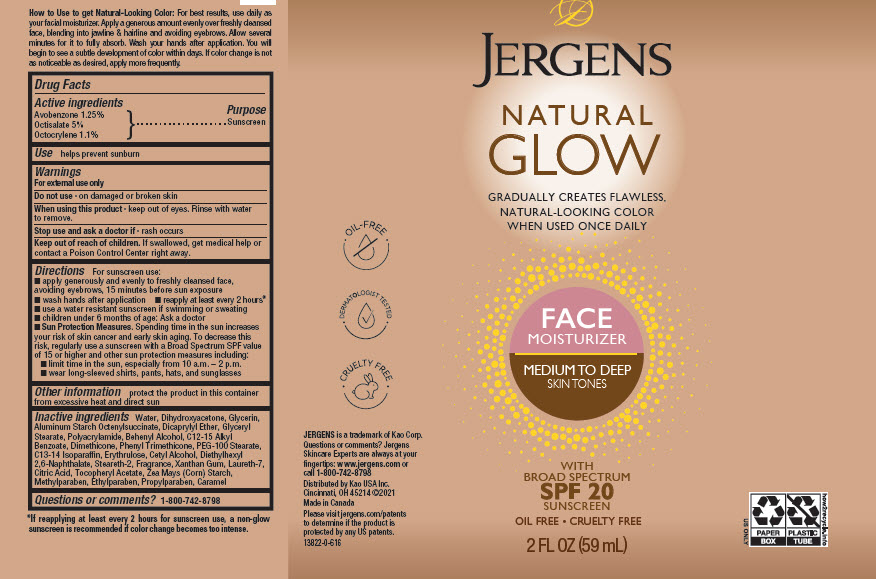 DRUG LABEL: Jergens Natural Glow Face
NDC: 10596-718 | Form: LOTION
Manufacturer: Kao USA Inc.
Category: otc | Type: HUMAN OTC DRUG LABEL
Date: 20250101

ACTIVE INGREDIENTS: AVOBENZONE 0.74 g/59 mL; OCTISALATE 2.95 g/59 mL; OCTOCRYLENE 0.65 g/59 mL
INACTIVE INGREDIENTS: WATER; GLYCERIN; STARCH, CORN; DIHYDROXYACETONE; CETYL ALCOHOL; DICAPRYLYL ETHER; GLYCERYL MONOSTEARATE; ALKYL (C12-15) BENZOATE; PHENYL TRIMETHICONE; DOCOSANOL; DIMETHICONE; METHYLPARABEN; PEG-100 STEARATE; DIETHYLHEXYL 2,6-NAPHTHALATE; STEARETH-2; POLYACRYLAMIDE (10000 MW); ETHYLPARABEN; C13-14 ISOPARAFFIN; PROPYLPARABEN; XANTHAN GUM; LAURETH-7; CITRIC ACID MONOHYDRATE; .ALPHA.-TOCOPHEROL ACETATE; L-ERYTHRULOSE; CARAMEL; ALUMINUM STARCH OCTENYLSUCCINATE

Jergens Natural Glow Face Moisturizer Medium to Deep skin tones with Broad Spectrum SPF20 sunscreen

Drug Facts

Active ingredients

Avobenzone 1.25%

Octisalate 5%

Octocrylene 1.1%

Purpose

Sunscreen

Use

helps prevent sunburn

Warnings

For external use only

Do not use on damaged or broken skin

When using this product keep out of eyes. Rinse with water to remove.

Stop use and ask a doctor if rash occurs

Keep out of reach of children. If swallowed, get medical help or contact a Poison Control Center right away.

Directions
For sunscreen use:

- apply generously and evenly to freshly cleansed face, avoiding eyebrows, 15 minutes before sun exposure
- wash hands after application
- reapply at least every 2 hours*
- use a water resistant sunscreen if swimming or sweating
- children under 6 months of age: Ask a doctor
- Sun Protection Measures: Spending time in the sun increases your risk of skin cancer and early skin aging. To decrease this risk, regularly use a sunscreen with a Broad Spectrum SPF value of 15 or higher and other sun protection measures including:
- limit time in the sun, especially from 10 a.m. - 2 p.m.
- wear long-sleeved shirts, pants, hats and sunglasses

Other information

protect the product in this container from excessive heat and direct sun

Inactive ingredients

Water, Dihydroxyacetone, Glycerin, Aluminum Starch Octenylsuccinate, Dicaprylyl Ether, Glyceryl Stearate, Polyacrylamide, Behebyk Alcohol, C12-15 Akyl Benzoate, Dimethicone, Phenyl Trimethicone, PEG-100 Stearate, C13-14 Isoparaffin, Erythrylose, Cetyl Alcohol, Diethylhexyl 2,6 Naphthalate, Steareth-2, Fragrance, Xanthan Gum, Laureth-7, Citric Acid, Fragrance, Tocopheryl Acetate, Zea Mays (Corn) Starch, Methylparaben, Ethylparaben, Propylparaben, Caramel

Questions or comments? 1-800-742-8798

How to Use to get Natural-Looking Color: For best results, use daily as your facial moisturizer. Apply a generous amount evenly over freshly cleansed face, blending into jawline & hairline and avoiding eyebrows. Allow several minutes for it to fully absorb. Wash your hands after application. You will begin to see development of color within several days with no sunless tanner odor. If color change is not as noticeable as desired, apply more frequently.

*If reapplying at least every 2 hours for sunscreen use, a non-glow sunscreen is recommended if color change becomes too intense.

www.jergens.com or call 1-800-742-8798

Distributed by Kao USA Inc., Cincinnati, OH 45214 ©2021

Made in Canada

PACKAGE LABEL

JERGENS®

NATURAL GLOW

GRADUALLY CREATES FLAWLESS, NATURAL-LOOKING COLOR WHEN USED ONCE DAILY

FACE MOISTURIZER

MEDIUM TO DEEP SKIN TONES

WITH BROAD SPECTRUM SPF 20 SUNSCREEN

OIL FREE • CRUELTY FREE

2 FL OZ (59 mL)